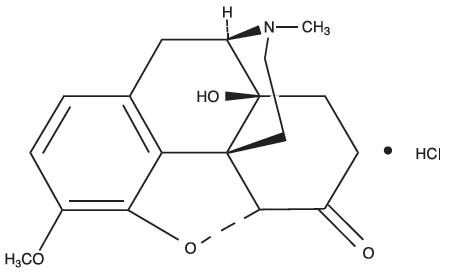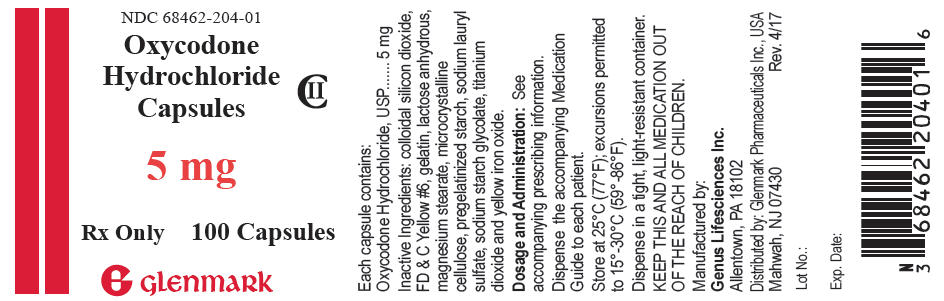 DRUG LABEL: Oxycodone Hydrochloride
NDC: 68462-204 | Form: CAPSULE
Manufacturer: Glenmark Pharmaceuticals, Inc
Category: prescription | Type: HUMAN PRESCRIPTION DRUG LABEL
Date: 20181212
DEA Schedule: CII

ACTIVE INGREDIENTS: Oxycodone Hydrochloride 5 mg/1 1
INACTIVE INGREDIENTS: Silicon Dioxide; Lactose, Unspecified Form; Magnesium Stearate; Microcrystalline Cellulose; Starch, Corn; Sodium Lauryl Sulfate; Sodium Starch Glycolate Type A Potato

HIGHLIGHTS OF PRESCRIBING INFORMATION

These highlights do not include all the information needed to use OXYCODONE HYDROCHLORIDE CAPSULES safely and effectively. See full prescribing information for OXYCODONE HYDROCHLORIDE CAPSULES.
Oxycodone Hydrochloride Capsules CII
Initial U.S. Approval: 1950

WARNING: ADDICTION, ABUSE, AND MISUSE; LIFE-THREATENING RESPIRATORY DEPRESSION; ACCIDENTAL INGESTION; NEONATAL OPIOID WITHDRAWAL SYNDROME; and CYTOCHROME P450 3A4 INTERACTION; and RISKS FROM CONCOMITANT USE WITH BENZODIAZEPINES OR OTHER CNS DEPRESSANTS

WARNING : RISK OF MEDICATION ERRORS; ADDICTION, ABUSE, AND MISUSE; LIFE-THREATENING RESPIRATORY DEPRESSION; ACCIDENTAL INGESTION; NEONATAL OPIOID WITHDRAWAL SYNDROME; CYTOCHROME P450 3A4 INTERACTION; and RISKS FROM CONCOMITANT USE WITH BENZODIAZEPINES OR OTHER CNS DEPRESSANTS

See full prescribing information for complete boxed warning.

- Oxycodone hydrochloride capsules exposes users to risks of addiction, abuse, and misuse, which can lead to overdose and death. Assess patient's risk before prescribing and monitor regularly for these behaviors and conditions. (5.1)
- Serious, life-threatening, or fatal respiratory depression may occur. Monitor closely, especially upon initiation or following a dose increase. (5.2)
- Accidental ingestion of oxycodone hydrochloride capsules, especially by children, can result in a fatal overdose of oxycodone. (5.2)
- Prolonged use of oxycodone hydrochloride capsules during pregnancy can result in neonatal opioid withdrawal syndrome, which may be life-threatening if not recognized and treated. If prolonged opioid use is required in a pregnant woman, advise the patient of the risk of neonatal opioid withdrawal syndrome and ensure that appropriate treatment will be available. (5.3)
- Concomitant use with CYP3A4 inhibitors (or discontinuation of CYP3A4 inducers) can result in a fatal overdose of oxycodone. (5.4, 7, 12.3)
- Concomitant use of opioids with benzodiazepines or other central nervous system (CNS) depressants, including alcohol, may result in profound sedation, respiratory depression, coma, and death. Reserve concomitant prescribing for use in patients for whom alternative treatment options are inadequate; limit dosages and durations to the minimum required; and follow patients for signs and symptoms of respiratory depression and sedation (5.5, 7)

RECENT MAJOR CHANGES

Boxed Warning | 12/2016
Indications And Usage | 12/2016
Dosage And Administration | 12/2016
Warnings And Precautions | 12/2016

1. INDICATIONS AND USAGE

Oxycodone hydrochloride capsule is an opioid agonist indicated for the management of pain severe enough to require an opioid analgesic and for which alternative treatments are inadequate. (1)

Limitations of Use (1)

Because of the risks of addiction, abuse, and misuse with opioids, even at recommended doses, reserve Oxycodone hydrochloride capsules for use in patients for whom alternative treatment options [e.g., non-opioid analgesics or opioid combination products];

- Have not been tolerated, or are not expected to be tolerated,
- Have not provided adequate analgesia, or are not expected to provide adequate analgesia

2. DOSAGE AND ADMINISTRATION

- Use the lowest effective dosage for the shortest duration consistent with individual patient treatment goals. (2.1)
- Individualize dosing based on the severity of pain, patient response, and prior analgesic experience, and risk factor for addiction, abuse, and misuse (2.1)
- Initiate dosing with a range of 5 to 15 mg every 4 to 6 hours as needed for pain. (2.2)
- For control of chronic pain, administer Oxycodone hydrochloride capsules on a regularly scheduled basis, at the lowest dosage level to achieve adequate analgesia. (2.2)
- Individually titrate Oxycodone hydrochloride capsules to a dose that provides adequate analgesia and minimizes adverse reactions. (2.3)
- Do not stop Oxycodone hydrochloride capsules abruptly in a physically dependent patient. (2.4)

3. DOSAGE FORMS AND STRENGTHS

Immediate-release capsules: 5 mg (3)

4. CONTRAINDICATIONS

- Significant respiratory depression. (4)
- Acute or severe bronchial asthma in an unmonitored setting or in absence of resuscitative equipment. (4)
- Known or suspected gastrointestinal obstruction, including paralytic ileus. (4)
- Hypersensitivity to oxycodone. (4)

5. WARNINGS AND PRECAUTIONS

- Life-Threatening Respiratory Depression in Patients with Chronic Pulmonary Disease or in Elderly, Cachectic or Debilitated Patients: Monitor closely, particularly during initiation and titration. (5.6)
- Adrenal Insufficiency: If diagnosed, treat with physiologic replacement of corticosteroids, and wean patient off of the opioid. (5.7)
- Severe Hypotension: Monitor during dosage initiation and titration. Avoid use of Oxycodone hydrochloride Capsules in patients with circulatory shock. (5.8)
- Risks of Use in Patients with Increased lntracranial Pressure, Brain Tumors, Head Injury, or Impaired Consciousness: Monitor for sedation and respiratory depression. Avoid use of Oxycodone Hydrochloride Capsules in patients with impaired consciousness or coma. (5.9)

6. ADVERSE REACTIONS

Most common adverse reactions are nausea, constipation, vomiting, headache, pruritus, insomnia, dizziness, asthenia, and somnolence. (6)

To report SUSPECTED ADVERSE REACTIONS, contact Pharm-Olam at 1-866-511-6754 or FDA at 1-800-FDA-1088 or www.fda.gov.medwatch.

7. DRUG INTERACTIONS

- Serotonergic Drugs: Concomitant use may result in serotonin syndrome. Discontinue Oxycodone Hydrochloride Capsules if serotonin syndrome is suspected. (7)
- Monoamine Oxidase Inhibitors (MAOIs): Can potentiate the effects of oxycodone. Avoid concomitant use in patients receiving MAOIs or within 14 days of stopping treatment with an MAOI. (7)
- Mixed Agonist/Antagonist and Partial Agonist Opioid Analgesics: Avoid use with Oxycodone Hydrochloride Capsules because they may reduce analgesic effect of Oxycodone Hydrochloride Capsules or precipitate withdrawal symptoms. (7)

8. USE IN SPECIFIC POPULATIONS

- Pregnancy: May cause fetal harm. (8.1)

FULL PRESCRIBING INFORMATION

WARNING: ADDICTION, ABUSE, AND MISUSE; LIFE-THREATENING RESPIRATORY DEPRESSION; ACCIDENTAL INGESTION; NEONATAL OPIOID WITHDRAWAL SYNDROME; and CYTOCHROME P450 3A4 INTERACTION; and RISKS FROM CONCOMITANT USE WITH BENZODIAZEPINES OR OTHER CNS DEPRESSANTS

Addiction, Abuse, and Misuse

Oxycodone hydrochloride capsules exposes patients and other users to risks of opioid addiction, abuse, and misuse, which can lead to overdose and death. Assess patient's risk prior to prescribing Oxycodone hydrochloride capsules and monitor all patients regularly for the development of these behaviors and conditions. [see Warnings and Precautions (5.1)].

Life-Threatening Respiratory Depression

Serious, life-threatening, or fatal respiratory depression may occur with use of Oxycodone hydrochloride capsules. Monitor for respiratory depression, especially during initiation of Oxycodone hydrochloride capsules or following a dose increase. [see Warnings and Precautions (5.2)].

Accidental Ingestion

Accidental ingestion of even one dose of Oxycodone hydrochloride capsules, especially by children, can result in a fatal overdose of oxycodone. [see Warnings and Precautions (5.2)].

Neonatal Opioid Withdrawal Syndrome

Prolonged use of Oxycodone hydrochloride capsules during pregnancy can result in neonatal opioid withdrawal syndrome, which may be life-threatening if not recognized and treated, and requires management according to protocols developed by neonatology experts. If opioid use is required for a prolonged period in a pregnant woman, advise the patient of the risk of neonatal opioid withdrawal syndrome and ensure that appropriate treatment will be available. [see Warnings and Precautions (5.3)].

Cytochrome P450 3A4 Interaction

The concomitant use of Oxycodone hydrochloride capsules with all cytochrome P450 3A4 inhibitors may result in an increase in oxycodone plasma concentrations, which could increase or prolong adverse reactions and may cause potentially fatal respiratory depression. In addition, discontinuation of a concomitantly used cytochrome P450 3A4 inducer may result in an increase in oxycodone plasma concentration. Monitor patients receiving Oxycodone hydrochloride capsules and any CYP3A4 inhibitor or inducer. [see Warnings and Precautions (5.4), Drug Interactions (7), Clinical Pharmacology (12.3)].

Risks From Concomitant Use With Benzodiazepines Or Other CNS Depressants

Concomitant use of opioids with benzodiazepines or other central nervous system (CNS) depressants, including alcohol, may result in profound sedation, respiratory depression, coma, and death [see Warnings and Precautions (5.5), Drug Interactions (7)].

- Reserve concomitant prescribing of Oxycodone hydrochloride capsules and benzodiazepines or other CNS depressants for use in patients for whom alternative treatment options are inadequate.
- Limit dosages and durations to the minimum required.
- Follow patients for signs and symptoms of respiratory depression and sedation.

1. INDICATIONS AND USAGE

Oxycodone hydrochloride capsule is an opioid agonist indicated for the management of pain severe enough to require an opioid analgesic and for which alternative treatments are inadequate.

Limitations of Use

Because of the risks of addiction, abuse, and misuse with opioids, even at recommended doses, [see Warnings and Precautions (5.1)], reserve Oxycodone hydrochloride capsules for use in patients for whom alternative treatment options [e.g., non-opioid analgesics or opioid combination products]:

- Have not been tolerated, or are not expected to be tolerated,
- Have not provided adequate analgesia, or are not expected to provide adequate analgesia

2. DOSAGE AND ADMINISTRATION

2.1 Important Dosage and Administration Instructions

Use the lowest effective dosage for the shortest duration consistent with individual patient treatment goals [see Warnings and Precautions (5)].

Initiate the dosing regimen for each patient individually, taking into account the patient's severity of pain, patient response, prior analgesic treatment experience, and risk factors for addiction, abuse, and misuse [see Warnings and Precautions (5.1)].

Monitor patients closely for respiratory depression, especially within the first 24-72 hours of initiating therapy and following dosage increases with Oxycodone hydrochloride capsules and adjust the dosage accordingly [see Warnings and Precautions (5.2)].

2.2 Initial Dosage

Use of Oxycodone hydrochloride capsules as the First Opioid Analgesic

Initiate treatment with Oxycodone hydrochloride capsules in a dosing range of 5 to 15 mg every 4 to 6 hours as needed for pain.

Conversion from Other Opioids to Oxycodone hydrochloride capsules

There is inter-patient variability in the potency of opioid drugs and opioid formulations. Therefore, a conservative approach is advised when determining the total daily dosage of Oxycodone Hydrochloride Capsules. It is safer to underestimate a patient's 24-hour Oxycodone Hydrochloride Capsules dosage than to overestimate the 24-hour Oxycodone Hydrochloride Capsules dosage and manage an adverse reaction due to overdose.

Conversion from Oxycodone hydrochloride capsules to Extended-Release Oxycodone Hydrochloride

The relative bioavailability of Oxycodone hydrochloride capsules compared to extended-release oxycodone is unknown, so conversion to extended-release tablets must be accompanied by close observation for signs of excessive sedation and respiratory depression.

2.3 Titration and Maintenance of Therapy

Individually titrate Oxycodone hydrochloride capsules to a dose that provides adequate analgesia and minimizes adverse reactions. Continually reevaluate patients receiving Oxycodone hydrochloride capsules to assess the maintenance of pain control and the relative incidence of adverse reactions, as well as monitoring for the development of addiction, abuse, or misuse [see Warnings and Precautions (5.1)]. Frequent communication is important among the prescriber, other members of the healthcare team, the patient, and the caregiver/family during periods of changing analgesic requirements, including initial titration.

If the level of pain increases after dosage stabilization, attempt to identify the source of increased pain before increasing the Oxycodone Hydrochloride Capsules dosage. If unacceptable opioid-related adverse reactions are observed, consider reducing the dosage.

Adjust the dosage to obtain an appropriate balance between management of pain and opioid-related adverse reactions.

2.4 Discontinuation of Oxycodone Hydrochloride Capsules

When a patient who has been taking Oxycodone hydrochloride capsules regularly and may be physically dependent no longer requires therapy with Oxycodone Hydrochloride Capsules, taper the dose gradually, by 25% to 50% every 2 to 4 days, while monitoring carefully for signs and symptoms of withdrawal. If the patient develops these signs or symptoms, raise the dose to the previous level and taper more slowly, either by increasing the interval between decreases, decreasing the amount of change in dose, or both. Do not abruptly discontinue Oxycodone hydrochloride capsules in a physically-dependent patient [see Warnings and Precautions (5.12), Drug Abuse and Dependence (9.3)].

3. DOSAGE FORMS AND STRENGTHS

Oxycodone Hydrochloride Capsules, USP

Capsules 5 mg: Each capsule has an opaque yellow cap imprinted in black ink with "LV" and an opaque white body imprinted in black ink with "901" containing 5 mg of oxycodone hydrochloride , USP.

4. CONTRAINDICATIONS

Oxycodone Hydrochloride capsule is contraindicated in patients with:

- Significant respiratory depression [see Warnings and Precautions (5.2)]
- Acute or severe bronchial asthma in an unmonitored setting or in the absence of resuscitative equipment [see Warnings and Precautions (5.6)]
- Known or suspected gastrointestinal obstruction, including paralytic ileus [see Warnings and Precautions (5.10)]
- Hypersensitivity to oxycodone (e.g., angioedema) [see Adverse Reactions (6)]

5. WARNINGS AND PRECAUTIONS

5.1 Addiction, Abuse, and Misuse

Oxycodone hydrochloride capsules contains oxycodone, a Schedule II controlled substance. As an opioid, Oxycodone Hydrochloride Capsules expose users to the risks of addiction, abuse, and misuse [see Drug Abuse and Dependence (9)].

Although the risk of addiction in any individual is unknown, it can occur in patients appropriately prescribed Oxycodone Hydrochloride Capsules. Addiction can occur at recommended dosages and if the drug is misused or abused.

Assess each patient's risk for opioid addiction, abuse, or misuse prior to prescribing Oxycodone Hydrochloride Capsules, and monitor all patients receiving Oxycodone Hydrochloride Capsules for the development of these behaviors and conditions. Risks are increased in patients with a personal or family history of substance abuse (including drug or alcohol abuse or addiction) or mental illness (e.g., major depression). The potential for these risks should not, however, prevent the proper management of pain in any given patient. Patients at increased risk may be prescribed opioids such as Oxycodone Hydrochloride Capsules, but use in such patients necessitates intensive counseling about the risks and proper use of Oxycodone Hydrochloride Capsules along with intensive monitoring for signs of addiction, abuse, and misuse.

Opioids are sought by drug abusers and people with addiction disorders and are subject to criminal diversion. Consider these risks when prescribing or dispensing Oxycodone Hydrochloride Capsules. Strategies to reduce these risks include prescribing the drug in the smallest appropriate quantity and advising the patient on the proper disposal of unused drug [see Patient Counseling Information (17)]. Contact local state professional licensing board or state controlled substances authority for information on how to prevent and detect abuse or diversion of this product.

5.2 Life-Threatening Respiratory Depression

Serious, life-threatening, or fatal respiratory depression has been reported with the use of opioids, even when used as recommended. Respiratory depression, if not immediately recognized and treated, may lead to respiratory arrest and death. Management of respiratory depression may include close observation, supportive measures, and use of opioid antagonists, depending on the patient's clinical status [see Overdosage (10)]. Carbon dioxide (CO2) retention from opioid-induced respiratory depression can exacerbate the sedating effects of opioids.

While serious, life-threatening, or fatal respiratory depression can occur at any time during the use of Oxycodone Hydrochloride Capsules, the risk is greatest during the initiation of therapy or following a dosage increase. Monitor patients closely for respiratory depression, especially within the first 24-72 hours of initiating therapy with and following dosage increases of Oxycodone Hydrochloride Capsules.

To reduce the risk of respiratory depression, proper dosing and titration of Oxycodone Hydrochloride Capsules are essential [see Dosage and Administration (2)]. Overestimating the Oxycodone Hydrochloride Capsules dosage when converting patients from another opioid product can result in a fatal overdose with the first dose.

Accidental ingestion of even one dose of Oxycodone Hydrochloride Capsules, especially by children, can result in respiratory depression and death due to an overdose of oxycodone.

5.3 Neonatal Opioid Withdrawal Syndrome

Prolonged use of Oxycodone Hydrochloride Capsules during pregnancy can result in withdrawal in the neonate. Neonatal opioid withdrawal syndrome, unlike opioid withdrawal syndrome in adults, may be life-threatening if not recognized and treated, and requires management according to protocols developed by neonatology experts. Observe newborns for signs of neonatal opioid withdrawal syndrome and manage accordingly. Advise pregnant women using opioids for a prolonged period of the risk of neonatal opioid withdrawal syndrome and ensure that appropriate treatment will be available [see Use in Specific Populations (8.I), Patient Counseling Information (17)].

5.4 Risks of Concomitant Use or Discontinuation of Cytochrome P450 3A4 Inhibitors and Inducers

Concomitant use of Oxycodone Hydrochloride Capsules with a CYP3A4 inhibitor, such as macrolide antibiotics (e.g., erythromycin), azole-antifungal agents (e.g., ketoconazole), and protease inhibitors (e.g., ritonavir), may increase plasma concentrations of oxycodone and prolong opioid adverse reactions, which may cause potentially fatal respiratory depression [see Warnings and Precautions(5.2)], particularly when an inhibitor is added after a stable dose of Oxycodone Hydrochloride Capsules is achieved. Similarly, discontinuation of a CYP3A4 inducer, such as rifampin, carbamazepine, and phenytoin, in Oxycodone Hydrochloride Capsules-treated patients may increase oxycodone plasma concentrations and prolong opioid adverse reactions. When using Oxycodone Hydrochloride Capsules with CYP3A4 inhibitors or discontinuing CYP3A4 inducers in Oxycodone Hydrochloride Capsules-treated patients, monitor patients closely at frequent intervals and consider dosage reduction of Oxycodone Hydrochloride Capsules until stable drug effects are achieved [see Dosage and Administration (2.1), Drug Interactions (7)].

Concomitant use of Oxycodone Hydrochloride Capsules with CYP3A4 inducers or discontinuation of an CYP3A4 inhibitor could decrease oxycodone plasma concentrations, decrease opioid efficacy or, possibly, lead to a withdrawal syndrome in a patient who had developed physical dependence to oxycodone. When using Oxycodone Hydrochloride Capsules with CYP3A4 inducers or discontinuing CYP3A4 inhibitors, monitor patients closely at frequent intervals and consider increasing the opioid dosage if needed to maintain adequate analgesia or if symptoms of opioid withdrawal occur [see Dosage and Administration (2.1), Drug Interactions (7)].

5.5 Risks from Concomitant Use with Benzodiazepines or Other CNS Depressants

Profound sedation, respiratory depression, coma, and death may result from the concomitant use of Oxycodone Hydrochloride Capsules with benzodiazepines or other CNS depressants (e.g., non-benzodiazepine sedatives/hypnotics, anxiolytics, tranquilizers, muscle relaxants, general anesthetics, antipsychotics, other opioids, alcohol). Because of these risks, reserve concomitant prescribing of these drugs for use in patients for whom alternative treatment options are inadequate.

Observational studies have demonstrated that concomitant use of opioid analgesics and benzodiazepines increases the risk of drug-related mortality compared to use of opioid analgesics alone. Because of similar pharmacological properties, it is reasonable to expect similar risk with the concomitant use of other CNS depressant drugs with opioid analgesics [see Drug Interactions (7)].

If the decision is made to prescribe a benzodiazepine or other CNS depressant concomitantly with an opioid analgesic, prescribe the lowest effective dosages and minimum durations of concomitant use. In patients already receiving an opioid analgesic, prescribe a lower initial dose of the benzodiazepine or other CNS depressant than indicated in the absence of an opioid, and titrate based on clinical response. If an opioid analgesic is initiated in a patient already taking a benzodiazepine or other CNS depressant, prescribe a lower initial dose of the opioid analgesic, and titrate based on clinical response. Follow patients closely for signs and symptoms of respiratory depression and sedation.

Advise both patients and caregivers about the risks of respiratory depression and sedation when Oxycodone Hydrochloride Capsules are used with benzodiazepines or other CNS depressants (including alcohol and illicit drugs). Advise patients not to drive or operate heavy machinery until the effects of concomitant use of the benzodiazepine or other CNS depressant have been determined. Screen patients for risk of substance use disorders, including opioid abuse and misuse, and warn them of the risk for overdose and death associated with the use of additional CNS depressants including alcohol and illicit drugs [see Drug Interactions (7) and Patient Counseling Information (17)].

5.6 Life-Threatening Respiratory Depression in Patients with Chronic Pulmonary Disease or in Elderly, Cachectic, or Debilitated Patients

The use of Oxycodone Hydrochloride Capsules in patients with acute or severe bronchial asthma in an unmonitored setting or in the absence of resuscitative equipment is contraindicated.

Patients with Chronic Pulmonary Disease: Oxycodone Hydrochloride Capsule-treated patients with significant chronic obstructive pulmonary disease or cor pulmonale, and those with a substantially decreased respiratory reserve, hypoxia, hypercapnia, or pre-existing respiratory depression are at increased risk of decreased respiratory drive including apnea, even at recommended dosages of Oxycodone Hydrochloride Capsules [see Warnings and Precautions (5.2)].

Elderly, Cachectic, or Debilitated Patients: Life-threatening respiratory depression is more likely to occur in elderly, cachectic, or debilitated patients because they may have altered pharmacokinetics or altered clearance compared to younger, healthier patients [see Warnings and Precautions (5.2].

Monitor such patients closely, particularly when initiating and titrating Oxycodone Hydrochloride Capsules and when Oxycodone Hydrochloride Capsules is given concomitantly with other drugs that depress respiration [see Warnings and Precautions (5.5)]. Alternatively, consider the use of non-opioid analgesics in these patients.

5.7 Adrenal Insufficiency

Cases of adrenal insufficiency have been reported with opioid use, more often following greater than one month of use. Presentation of adrenal insufficiency may include non specific symptoms and signs including nausea, vomiting, anorexia, fatigue, weakness, dizziness, and low blood pressure. If adrenal insufficiency is suspected, confirm the diagnosis with diagnostic testing as soon as possible. If adrenal insufficiency is diagnosed, treat with physiologic replacement doses of corticosteroids. Wean the patient off of the opioid to allow adrenal function to recover and continue corticosteroid treatment until adrenal function recovers. Other opioids may be tried as some cases reported use of a different opioid without recurrence of adrenal insufficiency. The information available does not identify any particular opioids as being more likely to be associated with adrenal insufficiency.

5.8 Severe Hypotension

Oxycodone hydrochloride capsules may cause severe hypotension including orthostatic hypotension and syncope in ambulatory patients. There is increased risk in patients whose ability to maintain blood pressure has already been compromised by a reduced blood volume or concurrent administration of certain CNS depressant drugs (e.g., phenothiazines or general anesthetics) [see Drug Interactions (7)]. Monitor these patients for signs of hypotension after initiating or titrating the dosage of Oxycodone Hydrochloride Capsules. In patients with circulatory shock, Oxycodone Hydrochloride Capsules may cause vasodilation that can further reduce cardiac output and blood pressure. Avoid the use of Oxycodone Hydrochloride Capsules in patients with circulatory shock.

5.9 Risks of Use in Patients with Increased Intracranial Pressure, Brain Tumors, Head Injury, or Impaired Consciousness

In patients who may be susceptible to the intracranial effects of CO2 retention (e.g., those with evidence of increased intracranial pressure or brain tumors), Oxycodone Hydrochloride Capsules may reduce respiratory drive, and the resultant CO2 retention can further increase intracranial pressure. Monitor such patients for signs of sedation and respiratory depression, particularly when initiating therapy with Oxycodone Hydrochloride Capsules.

Opioids may also obscure the clinical course in a patient with a head injury. Avoid the use of Oxycodone Hydrochloride Capsules in patients with impaired consciousness or coma.

5.10 Risks of Use in Patients with Gastrointestinal Conditions

Oxycodone Hydrochloride Capsules are contraindicated in patients with known or suspected gastrointestinal obstruction, including paralytic ileus.

The oxycodone in Oxycodone Hydrochloride Capsules may cause spasm of the sphincter of Oddi. Opioids may cause increases in serum amylase. Monitor patients with biliary tract disease, including acute pancreatitis, for worsening symptoms.

5.11 Increased Risk of Seizures in Patients with Seizure Disorders

The oxycodone in Oxycodone Hydrochloride Capsules may increase the frequency of seizures in patients with seizure disorders,and may increase the risk of seizures occurring in other clinical settings associated with seizures. Monitor patients with a history of seizure disorders for worsened seizure control during Oxycodone Hydrochloride Capsules therapy.

5.12 Withdrawal

Avoid the use of mixed agonist/antagonist (e.g., pentazocine, nalbuphine, and butorphanol) or partial agonist (e.g., buprenorphine) analgesics in patients who are receiving a full opioid agonist analgesic, including Oxycodone Hydrochloride Capsules. In these patients, mixed agonist/antagonist and partial agonist analgesics may reduce the analgesic effect and/or precipitate withdrawal symptoms [see Drug Interactions (7)].

When discontinuing Oxycodone Hydrochloride Capsules in a physically-dependent patient, gradually taper the dosage [see Dosage and Administration (2.4]. Do not abruptly discontinue Oxycodone Hydrochloride Capsules in these patients [see Drug Abuse and Dependence (9.3)].

5.13 Risks of Driving and Operating Machinery

Oxycodone hydrochloride capsules may impair the mental or physical abilities needed to perform potentially hazardous activities such as driving a car or operating machinery. Warn patients not to drive or operate dangerous machinery unless they are tolerant to the effects of Oxycodone Hydrochloride Capsules and know how they will react to the medication [see Patient Counseling Information (17)].

6. ADVERSE REACTIONS

The following serious adverse reactions are described, or described in greater detail, in other sections:

- Addition, Abuse, and Misuse [see Warnings and Precautions (5.1)]
- Life-Threatening Respiratory Depression [see Warnings and Precautions (5.2)]
- Neonatal Opioid Withdrawal Syndrome [see Warnings and Precautions (5.3)]
- Interactions with Benzodiazepines or Other CNS Depressants [see Warnings and Precautions (5.5)]
- Adrenal Insufficiency [see Warnings and Precautions (5.7)]
- Severe Hypotension [see Warnings and Precautions (5.8)]
- Gastrointestinal Adverse Reactions [see Warnings and Precautions (5.10)]
- Seizures [see Warnings and Precautions (5.11)]
- Withdrawal [see Warnings and Precautions (5.12)]

The following adverse reactions associated with the use of oxycodone were identified in clinical studies or postmarketing reports. Because some of these reactions were reported voluntarily from a population of uncertain size, it is not always possible to reliably estimate their frequency or establish a causal relationship to drug exposure.

Serious adverse reactions associated with oxycodone use included: respiratory depression, respiratory arrest, circulatory depression, cardiac arrest, hypotension, and/or shock.

The common adverse reactions seen on initiation of therapy with oxycodone are dose related and are typical opioid-related adverse reactions. The most frequent adverse events include nausea, constipation, vomiting, headache, and pruritus. The frequency of these reactions depended on several factors, including clinical setting, the patient's level of opioid tolerance, and host factors specific to the individual.

In all patients for whom dosing information was available (n=191) from the open-label and double-blind studies involving another formulation of immediate-release oxycodone, the following adverse events were recorded in oxycodone treated patients with an incidence ≥ 3%. In descending order of frequency, they were: nausea, constipation, vomiting, headache, pruritus, insomnia, dizziness, asthenia, and somnolence.

The other less frequently observed adverse reactions from opioid analgesics, including Oxycodone Hydrochloride Capsules included:

Body as a Whole: abdominal pain, accidental injury, allergic reaction, back pain, chills and fever, fever, flu syndrome, infection, neck pain, pain, photosensitivity reaction, and sepsis.

Cardiovascular: deep thrombophlebitis, heart failure, hemorrhage, hypotension, migraine, palpitation, and tachycardia.

Digestive: anorexia, diarrhea, dyspepsia, dysphagia, gingivitis, glossitis, and nausea and vomiting.

Hemic and Lymphatic: anemia and leukopenia.

Metabolic and Nutritional: edema, gout, hyperglycemia, iron deficiency anemia and peripheral edema.

Musculoskeletal: arthralgia, arthritis, bone pain, myalgia and pathological fracture.

Nervous: agitation, anxiety, confusion, dry mouth, hypertonia, hypesthesia, nervousness, neuralgia, personality disorder, tremor, and vasodilation.

Respiratory: bronchitis, cough increased, dyspnea, epistaxis, laryngismus, lung disorder, pharyngitis, rhinitis, and sinusitis.

Skin and Appendages: herpes simplex, rash, sweating, and urticaria.

Special Senses: amblyopia.

Urogenital: urinary tract infection

Serotonin syndrome: Cases of serotonin syndrome, a potentially life-threatening condition, have been reported during concomitant use of opioids with serotonergic drugs.

Adrenal insufficiency: Cases of adrenal insufficiency have been reported with opioid use, more often following greater than one month of use.

Anaphylaxis: Anaphylaxis has been reported with ingredients contained in Oxycodone Hydrochloride Capsules.

Androgen deficiency: Cases of androgen deficiency have occurred with chronic use of opioids [see Clinical Pharmacology (12.2)].

7. DRUG INTERACTIONS

Table 1 includes clinically significant drug interactions with Oxycodone Hydrochloride Capsules

Table 1: Clinically Significant Drug Interactions with Oxycodone Hydrochloride Capsules
Inhibitors of CYP3A4 and CYP2D6
Clinical Impact: | The concomitant use of Oxycodone Hydrochloride Capsules and CYP3A4 inhibitors can increase the plasma concentration of oxycodone, resulting in increased or prolonged opioid effects. These effects could be more pronounced with concomitant use of Oxycodone Hydrochloride Capsules and CYP206 and CYP3A4 inhibitors, particularly when an inhibitor is added after a stable dose of Oxycodone Hydrochloride Capsules is achieved [see Warnings and Precautions (5.4)]. After stopping a CYP3A4 inhibitor, as the effects of the inhibitor decline, the oxycodone plasma concentration will decrease [see Clinical Pharmacology (12.3)], resulting in decreased opioid efficacy or a withdrawal syndrome in patients who had developed physical dependence to oxycodone.
Intervention: | If concomitant use is necessary, consider dosage reduction of Oxycodone Hydrochloride Capsules until stable drug effects are achieved. Monitor patients for respiratory depression and sedation at frequent intervals. If a CYP3A4 inhibitor is discontinued, consider increasing the Oxycodone Hydrochloride Capsules dosage until stable drug effects are achieved. Monitor for signs of opioid withdrawal.
Examples | Macrolide antibiotics (e.g., erythromycin, azole-antifungal agents (e.g., ketoconazole), protease inhibitors (e.g., ritonavir)
CYP3A4 Inducers
Clinical Impact: | The concomitant use of Oxycodone Hydrochloride Capsules and CYP3A4 inducers can decrease the plasma concentration of oxycodone [see Clinical Pharmacology (12.3)], resulting in decreased efficacy or onset of a withdrawal syndrome in patients who have developed physical dependence to oxycodone [see Warnings and Precautions (5.4)]. After stopping a CYP3A4 inducer, as the effects of the inducer decline, the oxycodone plasma concentration will increase [see Clinical Pharmacology (12.3)], which could increase or prolong both the therapeutic effects and adverse reactions, and may cause serious respiratory depression.
Intervention: | If concomitant use is necessary, consider increasing the Oxycodone Hydrochloride Capsule dosage until stable drug effects are achieved. Monitor for signs of opioid withdrawal. If a CYP3A4 inducer is discontinued, consider Oxycodone Hydrochloride Capsule dosage reduction and monitor for signs of respiratory depression.
Examples | Rifampin, carbamazepine, phenytoin
Benzodiazepines and other Central Nervous System (CNS) Depressants
Clinical Impact: | Due to additive pharmacologic effect, the concomitant use of benzodiazepines or other CNS depressants including alcohol, increases the risk of respiratory depression, profound sedation, coma, and death.
Intervention: | Reserve concomitant prescribing of these drugs for use in patients for whom alternative treatment options are inadequate. Limit dosages and durations to the minimum required. Follow patients closely for signs of respiratory depression and sedation [see Warnings and Precautions (5.5)].
Examples | Benzodiazepines and other sedatives/hypnotics, anxiolytics, tranquilizers, muscle relaxants, general anesthetics, antipsychotics, other opioids, alcohol.
Serotonergic Drugs
Clinical Impact: | The concomitant use of opioids with other drugs that affect the serotonergic neurotransmitter system has resulted in serotonin.
Intervention: | If concomitant use is warranted, carefully observe the patient, particularly during treatment initiation and dose adjustment. Discontinue Oxycodone Hydrochloride Capsules if serotonin syndrome is suspected.
Examples | Selective serotonin reuptake inhibitors (SSRIs), serotonin and norepinephrine reuptake inhibitors (SNRIs), tricyclic antidepressants (TCAs), triptans, 5-HT3 receptor antagonists, drugs that affect the serotonin neurotransmitter system (e.g., mirtazapine, trazodone, tramadol), monoamine oxidase (MAO) inhibitors (those intended to treat psychiatric disorders and also others, such as linezolid and intravenous methylene blue).
Monoamine Oxidase Inhibitors (MAOIs)
Clinical Impact: | MAOI interactions with opioids may manifest as serotonin syndrome or opioid toxicity (e.g., respiratory depression, coma) [see Warnings and Precautions (5.2)].
Intervention: | The use of Oxycodone hydrochloride Capsules is not recommended for patients taking MAOIs or within 14 days of stopping such treatment. If urgent use of an opioid is necessary, use test doses and frequent titration of small doses to treat pain while closely monitoring blood pressure and signs and symptoms of CNS and respiratory depression.
Examples: | phenelzine, tranylcypromine, linezolid
Mixed Agonist/Antagonist and Partial Agonist Opioid Analgesics
Clinical Impact: | May reduce the analgesic effect of Oxycodone Hydrochloride Capsules and/or precipitate withdrawal symptoms.
Intervention: | Avoid concomitant use.
Examples | butorphanol, nalbuphine, pentazocine, buprenorphine
Muscle Relaxants
Clinical Impact: | Oxycodone may enhance the neuromuscular blocking action of skeletal muscle relaxants and produce an increased degree of respiratory depression.
Intervention: | Monitor patients for signs of respiratory depression that may be greater than otherwise expected and decrease the dosage of Oxycodone Hydrochloride Capsules and/or the muscle relaxant as necessary.
Diuretics
Clinical Impact: | Opioids can reduce the efficacy of diuretics by inducing the release of antidiuretic hormone.
Intervention: | Monitor patients for signs of diminished diuresis and/or effects on blood pressure and increase the dosage of the diuretic as needed .
Anticholinergic Drugs
Clinical Impact: | The concomitant use of anticholinergic drugs may increase risk of urinary retention and/or severe constipation,which may lead to paralytic ileus.
Intervention: | Monitor patients for signs of urinary retention or reduced gastric motility when Oxycodone Hydrochloride Capsules is used concomitantly with anticholinergic drugs.

8. USE IN SPECIFIC POPULATIONS

8.1 Pregnancy

Risk Summary

Prolonged use of opioid analgesics during pregnancy may cause neonatal opioid withdrawal syndrome [see Warnings and Precautions (5.3)]. Available data with Oxycodone Hydrochloride Capsules are insufficient to inform a drug-associated risk for major birth defects and miscarriage.

Animal reproduction studies with oral administrations of oxycodone hydrochloride in rats and rabbits during the period of organogenesis at doses 2.6 and 8.1 times, respectively, the human dose of 60 mg/day did not reveal evidence of teratogenicity or embryo-fetal toxicity. In several published studies, treatment of pregnant rats with oxycodone at clinically relevant doses and below, resulted in neurobehavioral effects in offspring [see Data]. Based on animal data, advise pregnant women of the potential risk to a fetus.

The background risk of major birth defects and miscarriage for the indicated population is unknown. All pregnancies have a background risk of birth defect, loss, or other adverse outcomes. In the U.S. general population, the estimated background risk of major birth defects and miscarriage in clinically recognized pregnancies is 2-4% and 15-20%, respectively.

Clinical Considerations

Fetal/Neonatal Adverse Reactions

Prolonged use of opioid analgesics during pregnancy for medical or nonmedical purposes can result in physical dependence in the neonate and neonatal opioid withdrawal syndrome shortly after birth.

Neonatal opioid withdrawal syndrome presents as irritability, hyperactivity and abnormal sleep pattern, high pitched cry, tremor, vomiting, diarrhea, and failure to gain weight. The onset, duration, and severity of neonatal opioid withdrawal syndrome vary based on the specific opioid used, duration of use, timing and amount of last maternal use, and rate of elimination of the drug by the newborn. Observe newborns for symptoms of neonatal opioid withdrawal syndrome and manage accordingly [see Warnings and Precautions (5.3)].

Labor or Delivery

Opioids cross the placenta and may produce respiratory depression and psycho-physiologic effects in neonates. An opioid antagonist, such as naloxone, must be available for reversal of opioid-induced respiratory depression in the neonate. Oxycodone Hydrochloride Capsules is not recommended for use in pregnant women during or immediately prior to labor, when other analgesic techniques are more appropriate. Opioid analgesics, including Oxycodone Hydrochloride Capsules, can prolong labor through actions which temporarily reduce the strength, duration, and frequency of uterine contractions. However, this effect is not consistent and may be offset by an increased rate of cervical dilation, which tends to shorten labor. Monitor neonates exposed to opioid analgesics during labor for signs of excess sedation and respiratory depression.

Data

Animal Data

In embryo-fetal development studies in rats and rabbits, pregnant animals received oral doses of oxycodone hydrochloride administered during the period of organogenesis up to 16 mg/kg/day and up 25 mg/kg/day, respectively. These studies revealed no evidence of teratogenicity or embryo-fetal toxicity due to oxycodone. The highest doses tested in rats and rabbits were equivalent to approximately 2.6 and 8.1 times an adult human dose of 60 mg/day, respectively, on a mg/m^2 basis. In published studies, offspring of pregnant rats administered oxycodone during gestation have been reported to exhibit neurobehavioral effects including altered stress responses, increased anxiety-like behavior (2 mg/kg/day IV from Gestation Day 8 to 21 and Postnatal Day 1, 3, and 5; 0.3-times an adult human dose of 60 mg/day, on a mg/m^2 basis) and altered learning and memory (15 mg/kg/day orally from breeding through parturition; 2.4 times an adult human dose of 60 mg/day, on a mg/m^2 basis).

8.2 Lactation

Risk Summary

Oxycodone is present in breast milk. Published lactation studies report variable concentrations of oxycodone in breast milk with administration of immediate-release oxycodone to nursing mothers in the early postpartum period. The lactation studies did not assess breastfed infants for potential adverse reactions. Lactation studies have not been conducted with Oxycodone Hydrochloride Capsules, and no information is available on the effects of the drug on the breastfed infant or the effects of the drug on milk production.

The developmental and health benefits of breastfeeding should be considered along with the mother's clinical need for Oxycodone Hydrochloride Capsules and any potential adverse effects on the breastfed infant from Oxycodone Hydrochloride Capsules or from the underlying maternal condition.

Clinical Considerations

Monitor infants exposed to Oxycodone Hydrochloride Capsules through breast milk for excess sedation and respiratory depression. Withdrawal symptoms can occur in breastfed infants when maternal administration of an opioid analgesic is stopped, or when breast feeding is stopped.

8.3 Females and Males of Reproductive Potential

Infertility

Chronic use of opioids may cause reduced fertility in females and males of reproductive potential. It is not known whether these effects on fertility are reversible [see Adverse Reactions (6), Clinical Pharmacology (12.2)].

8.4 Pediatric Use

The safety and effectiveness and the pharmacokinetics of Oxycodone Hydrochloride Capsules in pediatric patients below the age of 18 have not been established.

8.5 Geriatric Use

Elderly patients (aged 65 years or older) may have increased sensitivity to oxycodone. In general, use caution when selecting a dose for an elderly patient, usually starting at the low end of the dosing range, reflecting the greater frequency of decreased hepatic, renal, or cardiac function and of concomitant disease or other drug therapy.

Respiratory depression is the chief risk for elderly patients treated with opioids, and has occurred after large initial doses were administered to patients who were not opioid-tolerant or when opioids were co-administered with other agents that depress respiration. Titrate the dosage of Oxycodone Hydrochloride Capsules slowly in geriatric patients and monitor closely for signs of central nervous system and respiratory depression [see Warnings and Precautions (5.6)].

Oxycodone is known to be substantially excreted by the kidney, and the risk of adverse reactions to this drug may be greater in patients with impaired renal function. Because elderly patients are more likely to have decreased renal function, care should be taken in dose selection, and it may be useful to monitor renal function.

8.6 Hepatic Impairment

Since oxycodone is extensively metabolized in the liver, its clearance may decrease in patients with hepatic impairment. Initiate therapy in these patients with a lower than usual dosage of Oxycodone Hydrochloride Capsules and titrate carefully. Monitor closely for adverse events such as respiratory depression, sedation, and hypotension [see Clinical Pharmacology (12.3)].

8.7 Renal Impairment

Information from oxycodone tablets indicate that patients with renal impairment had higher plasma concentrations of oxycodone than subjects with normal renal function. Initiate therapy with a lower than usual dosage of Oxycodone Hydrochloride Capsules and titrate carefully. Monitor closely for adverse events such as respiratory depression, sedation, and hypotension [see Clinical Pharmacology (12.3)].

9. DRUG ABUSE AND DEPENDENCE

9.1 Controlled Substance

Oxycodone hydrochloride capsules contains oxycodone, a Schedule II controlled substance

9.2 Abuse

Oxycodone hydrochloride capsules contains oxycodone, a substance with a high potential for abuse similar to other opioids including fentanyl, hydrocodone, hydromorphone, methadone, morphine, oxymorphone, and tapentadol. Oxycodone Hydrochloride Capsules can be abused and is subject to misuse, addiction, and criminal diversion [see Warnings and Precautions(5.1)].

All patients treated with opioids require careful monitoring for signs of abuse and addiction, because use of opioid analgesic products carries the risk of addiction even under appropriate medical use.

Prescription drug abuse is the intentional non-therapeutic use of a prescription drug, even once, for its rewarding psychological or physiological effects.

Drug addiction is a cluster of behavioral, cognitive, and physiological phenomena that develop after repeated substance use and includes: a strong desire to take the drug, difficulties in controlling its use, persisting in its use despite harmful consequences, a higher priority given to drug use than to other activities and obligations, increased tolerance, and sometimes a physical withdrawal.

"Drug-seeking" behavior is very common in persons with substance use disorders. Drug seeking tactics include emergency calls or visits near the end of office hours, refusal to undergo appropriate examination, testing, or referral, repeated "loss" of prescriptions, tampering with prescriptions, and reluctance to provide prior medical records or contact information for other treating health care provider(s). "Doctor shopping" (visiting multiple prescribers to obtain additional prescriptions) is common among drug abusers and people suffering from untreated addiction. Preoccupation with achieving adequate pain relief can be appropriate behavior in a patient with poor pain control.

Abuse and addiction are separate and distinct from physical dependence and tolerance. Health care providers should be aware that addiction may not be accompanied by concurrent tolerance and symptoms of physical dependence in all addicts. In addition, abuse of opioids can occur in the absence of true addiction.

Oxycodone Hydrochloride Capsules, like other opioids, can be diverted for non-medical use into illicit channels of distribution. Careful record-keeping of prescribing information, including quantity, frequency, and renewal requests, as required by state and federal law, is strongly advised.

Proper assessment of the patient, proper prescribing practices, periodic re-evaluation of therapy, and proper dispensing and storage are appropriate measures that help to limit abuse of opioid drugs.

Risks Specific to Abuse of Oxycodone Hydrochloride Capsules

Oxycodone Hydrochloride Capsules are for oral use only. Abuse of oxycodone poses a risk of overdose and death. The risk is increased with concurrent abuse of alcohol and other central nervous system depressants.

Parenteral drug abuse is commonly associated with transmission of infectious diseases such as hepatitis and HIV.

9.3 Dependence

Both tolerance and physical dependence can develop during chronic opioid therapy. Tolerance is the need for increasing doses of opioids to maintain a defined effect such as analgesia (in the absence of disease progression or other external factors). Tolerance may occur to both the desired and undesired effects of drugs, and may develop at different rates for different effects.

Physical dependence results in withdrawal symptoms after abrupt discontinuation or a significant dosage reduction of a drug. Withdrawal also may be precipitated through the administration of drugs with opioid antagonist activity (e.g., naloxone, nalmefene), mixed agonist/antagonist analgesics (e.g., pentazocine, butorphanol, nalbuphine), or partial agonists (e.g., buprenorphine). Physical dependence may not occur to a clinically significant degree until after several days to weeks of continued opioid usage.

Oxycodone hydrochloride capsules should not be abruptly discontinued in a physically dependent patient [see Dosage and Administration(2.4)]. If Oxycodone Hydrochloride Capsules are abruptly discontinued in a physically-dependent patient, a withdrawal syndrome may occur. Some or all of the following can characterize this syndrome: restlessness, lacrimation, rhinorrhea, yawning, perspiration, chills, myalgia, and mydriasis. Other signs and symptoms also may develop, including irritability, anxiety, backache, joint pain, weakness, abdominal cramps, insomnia, nausea, anorexia, vomiting, diarrhea, or increased blood pressure, respiratory rate, or heart rate.

Infants born to mothers physically dependent on opioids will also be physically dependent and may exhibit respiratory difficulties and withdrawal signs [see Use in Specific Populations (8.1)].

10. OVERDOSAGE

Clinical Presentation

Acute overdose with Oxycodone hydrochloride capsules can be manifested by respiratory depression, somnolence progressing to stupor or coma, skeletal muscle flaccidity, cold and clammy skin, constricted pupils, and, in some cases, pulmonary edema, bradycardia, hypotension, partial or complete airway obstruction, atypical snoring, and death. Marked mydriasis rather than miosis may be seen with hypoxia in overdose situations [see Clinical Pharmacology (12.2)].

Treatment of Overdose

In case of overdose, priorities are the reestablishment of a patent and protected airway and institution of assisted or controlled ventilation, if needed. Employ other supportive measures (including oxygen and vasopressors) in the management of circulatory shock and pulmonary edema as indicated. Cardiac arrest or arrhythmias will require advanced life-support techniques.

The opioid antagonists, naloxone or nalmefene, are specific antidotes to respiratory depression resulting from opioid overdose. For clinically significant respiratory or circulatory depression secondary to oxycodone overdose, administer an opioid antagonist. Opioid antagonists should not be administered in the absence of clinically significant respiratory or circulatory depression secondary to oxycodone overdose.

Because the duration of opioid reversal is expected to be less than the duration of action of oxycodone in Oxycodone Hydrochloride Capsules, carefully monitor the patient until spontaneous respiration is reliably re-established. If the response to an opioid antagonist is suboptimal or only brief in nature, administer additional antagonist as directed by the product's prescribing information.

In an individual physically dependent on opioids, administration of the recommended usual dosage of the antagonist will precipitate an acute withdrawal syndrome. The severity of the withdrawal symptoms experienced will depend on the degree of physical dependence and the dose of the antagonist administered. If a decision is made to treat serious respiratory depression in the physically dependent patient, administration of the antagonist should be initiated with care and by titration with smaller than usual doses of the antagonist.

11. DESCRIPTION

Oxycodone hydrochloride capsule is an agonist, available as a hard gelatin capsule 5 mg for oral administration. The chemical name is (5R,9R,13S,14S)-4,5α-epoxy-14-hydroxy-3-methoxy-17-methylmorphinan-6-one hydrochloride. The molecular weight is 351.82.

Its molecular formula is C18H21NO4HCl, and it has the following chemical structure.

Oxycodone hydrochloride is a white, odorless crystalline powder derived from the opium alkaloid, thebaine. It is soluble in water and slightly soluble in alcohol.

The inactive ingredients in Oxycodone Hydrochloride Capsules, 5 mg include: colloidal silicon dioxide, FD&C Yellow #6, gelatin, lactose anhydrous, magnesium stearate, microcrystalline cellulose, pregelatinized starch, sodium lauryl sulfate, sodium starch glycolate, titanium dioxide and yellow iron oxide. The imprinting on the hard gelatin capsule is black ink.

12. CLINICAL PHARMACOLOGY

12.1 Mechanism of Action

Oxycodone is a full opioid agonist and is relatively selective for the mu-opioid receptor, although it can bind to other opioid receptors at higher doses. The principal therapeutic action of oxycodone is analgesia. Like all full opioid agonists, there is no ceiling effect for analgesia with oxycodone. Clinically, dosage is titrated to provide adequate analgesia and may be limited by adverse reactions, including respiratory and CNS depression.

The precise mechanism of the analgesic action is unknown. However, specific CNS opioid receptors for endogenous compounds with opioid-like activity have been identified throughout the brain and spinal cord and are thought to play a role in the analgesic effects of this drug.

12.2Pharmacodynamics

Effects on the Central Nervous System (CNS)

Oxycodone produces respiratory depression by direct action on brain stem respiratory centers. The respiratory depression involves a reduction in the responsiveness of the brain stem respiratory centers to both increases in carbon dioxide tension and electrical stimulation.

Oxycodone causes miosis, even in total darkness. Pinpoint pupils are a sign of opioid overdose but are not pathognomonic (e.g., pontine lesions of hemorrhagic or ischemic origins may produce similar findings). Marked mydriasis rather than miosis may be seen due to hypoxia in overdose situations.

Effects on the Gastrointestinal Tract and Other Smooth Muscle

Oxycodone causes a reduction in motility associated with an increase in smooth muscle tone in the antrum of the stomach and duodenum. Digestion of food in the small intestine is delayed and propulsive contractions are decreased. Propulsive peristaltic waves in the colon are decreased, while tone may be increased to the point of spasm, resulting in constipation. Other opioid-induced effects may include a reduction in biliary and pancreatic secretions, spasm of sphincter of Oddi, and transient elevations in serum amylase.

Effects on the Cardiovascular System

Oxycodone produces peripheral vasodilation which may result in orthostatic hypotension or syncope. Manifestations of histamine release and/or peripheral vasodilation may include pruritus, flushing, red eyes, sweating, and/or orthostatic hypotension.

Effects on the Endocrine System

Opioids inhibit the secretion of adrenocorticotropic hormone (ACTH), cortisol, and luteinizing hormone (LH) in humans [see Adverse Reactions (6)]. They also stimulate prolactin, growth hormone (OH) secretion, and pancreatic secretion of insulin and glucagon.

Chronic use of opioids may influence the hypothalamic-pituitary-gonadal axis, leading to androgen deficiency that may manifest as low libido, impotence, erectile dysfunction, amenorrhea, or infertility. The causal role of opioids in the clinical syndrome of hypogonadism is unknown because the various medical, physical, lifestyle, and psychological stressors that may influence gonadal hormone levels have not been adequately controlled for in studies conducted to date [see Adverse Reactions (6)].

Effects on the Immune System

Opioids have been shown to have a variety of effects on components of the immune system in in-vitro and animal models. The clinical significance of these findings is unknown. Overall, the effects of opioids appear to be modestly immunosuppressive.

Concentration-Efficacy Relationships

The minimum effective analgesic concentration will vary widely among patients, especially among patients who have been previously treated with potent agonist opioids. The minimum effective analgesic concentration of oxycodone for any individual patient may increase over time due to an increase in pain, the development of a new pain syndrome and/or the development of analgesic tolerance [see Dosage and Administration (2.1, 2.2)].

Concentration-Adverse Reaction Relationships

There is a relationship between increasing oxycodone plasma concentration and increasing frequency of dose-related opioid adverse reactions such as nausea, vomiting, CNS effects, and respiratory depression. In opioid-tolerant patients, the situation may be altered by the development of tolerance to opioid-related adverse reactions [see Dosage and Administration (2.1, 2.2, 2.3)].

12.3 Pharmacokinetics

The activity of oxycodone hydrochloride is primarily due to the parent drug oxycodone.

Absorption

About 60 to 87% of an oral dose reaches the systemic circulation in comparison to a parenteral dose. This high oral bioavailability (compared to other opioids) is due to lower pre-systemic and/or first-pass metabolism of oxycodone.

Food Effect

When Oxycodone hydrochloride capsules are administered with a high-fat meal, mean AUC values are increased by 23% and peak concentrations are decreased by 14%. Food causes a delay in Tmax (l.00 to 3 hours). Similar effects of food are expected with the oral solution.

Distribution

Following intravenous administration, the volume of distribution (Vss) for oxycodone was 2.6 L/kg. Plasma protein binding of oxycodone at 37°C and a pH of 7.4 was about 45%. Oxycodone has been found in breast milk.

Elimination

Metabolism

Oxycodone hydrochloride is extensively metabolized by multiple metabolic pathways to noroxycodone, oxymorphone, and noroxymorphone, which are subsequently glucuronidated. CYP3A4 mediated N-demethylation to noroxycodone is the primary metabolic pathway of oxycodone with a less contribution from CYP2D6 mediated 0-demethylation to oxymorphone.

Therefore, the formation of these and related metabolites can, in theory, be affected by other drugs. The major circulating metabolite is noroxycodone with an AUC ratio of 0.6 relative to that of oxycodone. Noroxycodone is reported to be a considerably weaker analgesic than oxycodone. Oxymorphone, although possessing analgesic activity, is present in the plasma only in low concentrations. The correlation between oxymorphone concentrations and opioid effects was much less than that seen with oxycodone plasma concentrations. The analgesic activity profile of other metabolites is not known.

Excretion

Oxycodone and its metabolites are excreted primarily via the kidney. The amounts measured in the urine have been reported as follows: free oxycodone up to 19%; conjugated oxycodone up to 50%; free oxymorphone 0%; conjugated oxymorphone < 14%; both free and conjugated noroxycodone have been found in the urine but not quantified. The total plasma clearance was 0.8 L/min for adults. Apparent elimination half-life of oxycodone following the administration of oxycodone is approximately 4 hours.

Specific Populations

Age: Geriatric Population:

Information obtained from oxycodone tablets indicate that the plasma concentrations of oxycodone did not appear to be increased in patients over of the age of 65.

Hepatic Impairment:

Because oxycodone is extensively metabolized in the liver, its clearance may decrease in hepaticimpaired patients. A dose adjustment is recommended in these patients [see Use in Specific Populations(8.6)].

Renal Impairment:

Because this drug is known to be substantially excreted by the kidney, and the risk of adverse reactions to this drug may be greater in patients with impaired renal function, a dose reduction is recommended for renal impaired patients [see Use in Specific Populations (8.7)].

Drug Interaction Studies

CYP3A4 Inhibitors

CYP3A4 is the major enzyme involved in noroxycodone formation. A published study showed that the co-administration of voriconazole, a CYP3A4 inhibitor, increased oxycodone AUC and Cmax by 3.6 and 1.7 fold, respectively.

CYP3A4 Inducers

A published study showed that the co-administration of rifampin, a drug metabolizing enzyme inducer, decreased oxycodone AUC and Cmax values by 86% and 63%, respectively.

CYP2D6 Inhibitors

Oxycodone is metabolized in part to oxymorphone via the cytochrome P450 isoenzyme CYP2D6. While this pathway may be blocked by a variety of drugs (e.g., certain cardiovascular drugs and antidepressants), such blockade has not yet been shown to be of clinical significance with this agent.

13. NONCLINICAL TOXICOLOGY

13.1 Carcinogenesis, Mutagenesis, Impairment of Fertility

Carcinogenesis

Long-term studies in animals to evaluate the carcinogenic potential of oxycodone hydrochloride have not been conducted.

Mutagenesis

Oxycodone hydrochloride was genotoxic in an in-vitro mouse lymphoma assay in the presence of metabolic activation. There was no evidence of genotoxic potential in an in-vitro bacterial reverse mutation assay (Salmonella typhimurium and Escherichia coli) and in an assay for chromosomal aberrations (in-vivo mouse bone marrow micronucleus assay).

Impairment of Fertility

Studies in animals to evaluate the potential impact of oxycodone on fertility have not been conducted.

16. HOW SUPPLIED/STORAGE AND HANDLING

Oxycodone hydrochloride capsule 5 mg is a hard gelatin capsule with an opaque yellow cap imprinted in black ink with "LV" and an opaque white body imprinted in black ink with "901" supplied as:

NDC# 68462-204-01: Bottle of 100 Capsules

STORAGE AND HANDLING

Dispense in a tight, light-resistant container. Protect from moisture and light.

Store at 25°C (77°F); excursions are permitted to 15° to 30°C (59° to 86°F) [see USP Controlled Room Temperature].

17. PATIENT COUNSELING INFORMATION

Advise the patient to read the FDA-approved patient labeling (Medication Guide).

Addiction, Abuse, and Misuse

Inform patients that the use of Oxycodone hydrochloride capsules, even when taken as recommended, can result in addiction, abuse, and misuse, which can lead to overdose and death [see Warnings and Precautions (5.1)]. Instruct patients not to share Oxycodone Hydrochloride Capsules with others and to take steps to protect Oxycodone Hydrochloride Capsules from theft or misuse.

Life-Threatening Respiratory Depression

Inform patients of the risk of life-threatening respiratory depression, including information that the risk is greatest when starting Oxycodone Hydrochloride Capsules or when the dosage is increased, and that it can occur even at recommended dosages [see Warnings and Precautions (5.2)]. Advise patients how to recognize respiratory depression and to seek medical attention if breathing difficulties develop.

Accidental Ingestion

Inform patients that accidental ingestion, especially by children, may result in respiratory depression or death [see Warnings and Precautions (5.2)]. Instruct patients to take steps to store Oxycodone Hydrochloride Capsules securely and to dispose of unused Oxycodone Hydrochloride Capsules by flushing down the toilet.

Interactions with Benzodiazepines and Other CNS Depressants

Inform patients and caregivers that potentially fatal additive effects may occur if Oxycodone Hydrochloride Capsules are used with benzodiazepines or other CNS depressants, including alcohol, and not to use these concomitantly unless supervised by a health care provider [see Warnings and Precautions (5.5), Drug Interactions (7)].

Serotonin Syndrome

Inform patients that opioids could cause a rare but potentially life-threatening condition resulting from concomitant administration of serotonergic drugs. Warn patients of the symptoms of serotonin syndrome and to seek medical attention right away if symptoms develop. Instruct patients to inform their healthcare providers if they are taking, or plan to take serotonergic medications. [see Drug Interactions (7)].

MAOI Interaction

Inform patients to avoid taking Oxycodone Hydrochloride Capsules while using any drugs that inhibit monoamine oxidase. Patients should not start MAOIs while taking Oxycodone Hydrochloride Capsules [see Drug Interactions (7)]

Adrenal Insufficiency

Inform patients that opioids could cause adrenal insufficiency, a potentially life threatening condition. Adrenal insufficiency may present with non-specific symptoms and signs such as nausea, vomiting, anorexia, fatigue, weakness, dizziness, and low blood pressure. Advise patients to seek medical attention if they experience a constellation of these symptoms [see Warnings and Precautions (5.7)].

Important Administration Instructions

Instruct patients how to properly take Oxycodone hydrochloride capsules. Patients should be advised not to adjust the dose of Oxycodone Hydrochloride Capsules without consulting the prescribing healthcare provider [see Dosage and Administration (2.1)]

If patients have been receiving treatment with Oxycodone Hydrochloride Capsules for more than a few weeks and cessation of therapy is indicated, counsel them on the importance of safely tapering the dose as abrupt discontinuation of the medication could precipitate withdrawal symptoms. Provide a dose schedule to accomplish a gradual discontinuation of the medication [see Dosage and Administration (2.4)].

Hypotension

Inform patients that Oxycodone hydrochloride capsules may cause orthostatic hypotension and syncope. Instruct patients how to recognize symptoms of low blood pressure and how to reduce the risk of serious consequences should hypotension occur (e.g., sit or lie down, carefully rise from a sitting or lying position) [see Warnings and Precautions (5.8)].

Anaphylaxis

Inform patients that anaphylaxis has been reported with ingredients contained in Oxycodone Hydrochloride Capsules. Advise patients how to recognize such a reaction and when to seek medical attention [Adverse Reactions (6)].

Pregnancy

Neonatal Opioid Withdrawal Syndrome

Inform female patients of reproductive potential that prolonged use of Oxycodone Hydrochloride Capsules during pregnancy can result in neonatal opioid withdrawal syndrome, which may be life-threatening if not recognized and treated [see Warnings and Precautions (5.3), Use in Specific Populations (8.1)].

Embryo-Fetal Toxicity

Inform female patients of reproductive potential that Oxycodone Hydrochloride Capsules can cause fetal harm and to inform the healthcare provider of a known or suspected pregnancy [see Use in Specific Populations (8.1)].

Lactation

Advise nursing mothers to monitor infants for increased sleepiness (more than usual), breathing difficulties, or limpness. Instruct nursing mothers to seek immediate medical care if they notice these signs [see Use in Specific Populations (8.2)].

Infertility

Inform patients that chronic use of opioids may cause reduced fertility. It is not known whether these effects on fertility are reversible [see Use in Specific Populations (8.3)].

Driving or Operating Heavy Machinery

Inform patients that Oxycodone hydrochloride capsules may impair the ability to perform potentially hazardous activities such as driving a car or operating heavy machinery. Advise patients not to perform such tasks until they know how they will react to the medication [see Warnings and Precautions (5.13)].

Constipation

Advise patients of the potential for severe constipation, including management instructions and when to seek medical attention [see Adverse Reactions (6), Clinical Pharmacology (12.2)].

Disposal of Unused Oxycodone hydrochloride capsules

Advise patients to dispose of unused Oxycodone hydrochloride capsules by flushing the capsules down the toilet or disposing of in accordance with local guidelines and/or regulations.

Manufactured by:
Genus Lifesciences Inc.
514 North 12th Street, Allentown, PA 18102

Distributed by:
Glenmark Pharmaceuticals Inc., USA
750 Corporate Drive, Mahwah, NJ 07430

PRINCIPAL DISPLAY PANEL - 5 mg Capsule Bottle Label

NDC 68462-204-01

Oxycodone
Hydrochloride
Capsules
CII

5 mg

Rx Only
100 Capsules

Glenmark